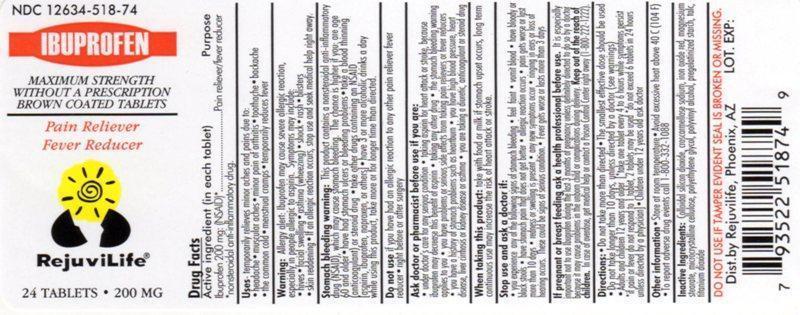 DRUG LABEL: Ibuprofen 
NDC: 12634-518 | Form: TABLET
Manufacturer: Apotheca, Inc
Category: prescription | Type: HUMAN PRESCRIPTION DRUG LABEL
Date: 20140303

ACTIVE INGREDIENTS: IBUPROFEN 200 mg/1 1
INACTIVE INGREDIENTS: COLLOIDAL SILICON DIOXIDE; CROSCARMELLOSE SODIUM; FERRIC OXIDE RED; MAGNESIUM STEARATE; CELLULOSE, MICROCRYSTALLINE; TALC; TITANIUM DIOXIDE

Ibuprofen Tablets, USP 200mg (NSAID)

ACTIVE INGREDIENT

Ibuprofen 200 mg (NSAID)*

* nonstreoidal anti-inflammatory drug

PURPOSE

Pain reliever / fever reducer

Use(s)

temporarily relieves minor aches and pain due to :
backache
headache
menstrual cramps
minor pain of arthritis
muscular aches
the common cold
toothache
temporarily reduces fever

WARNINGS

Allergy alerts: Ibuprofen may cause a severe allergy reaction, especially in people allergic to aspirin.
Symptoms may include:

- asthma (wheezing)
- blisters
- facial swelling
- hives
- rash
- shock
- skin reddening

If an allergic reaction occurs, stop use and seek medical help right away.
Stomach bleeding warning: This product contains a nonsteroidal anti-inflammatory drug (NSAID), which may cause stomach bleeding. The chance is higher if you:

- are age 60 or older
- have bad stomach ulcers or bleeding problems
- take a blood thinning (anticoagulant) or steroid drug
- take other drug containing prescription NSAID (aspirin, ibuprofen, naproxen, or others)
- have 3 or more alcoholic drinks every day while using this product
- the more or for a longer time than directed

DO NOT USE

- if you have ever had an allergic reaction to any other pain reliever/fever reducer
- right before or after heart surgery

ASK DOCTOR/PHARMACIST

Ask a doctor before use if you have

- problems or serious side effects from taking pain relievers or fever reducers
- stomach problems that last or come back, such as heartburn, upset stomach, or stomach pain
- ulcers
- bleeding problems
- high blood pressure
- heart or kidney disease
- taken a diuretics
- reached age 60 or older

Ask a doctor or pharmacist before use if you are

- taking any other drugs containg an NSAID (prescription or nonprescription)
- taking a blood thining (anticoagulant) or steriod drug
- under a doctor’s care for any serious condition
- taking aspirin for heart attacks or stroke, because ibuprofen may decrease this benefit of aspirin
- taking any other drug

When using this product

- take with food or milk if stomach upset occurs
- long term continuous use may increase the risk of heart attack or stroke

Stop use and ask doctor if

- you feel faint, vomit blood, or have bloody or black stools

These are signs of stomach bleeding.

- pain gets worse or lasts more than 10 days
- fever gets worse or lasts more than 3 days
- stomach pain or upset gets worse or lasts
- redness or swelling is present in painful area
- any new symptoms appear

PREGNACNCY OR BREAST FEEDING

Ask a health professional before use. It is especially important not to use ibuprofen during the last 3 months of pregnancy unless definitely directed to do so by a doctor because it may cause a problems in the unborn child or complications during delivery.

KEEP OUT OF REACH OF CHILDREN

In case of overdose, get medical help or contact a PoisonControlCenter right away. (1-800-222-1222)

INACTIVE INGREDIENTS

colloidal silicon dioxide, croscarmellose sodium, iron oxide red, magnesium stearate, microcrystalline cellulose, polyethylene glycol, polyvinyl alcohol, pregelatinised starch, talc, titanium dioxide.

QUESTIONS

Directions

- do not take more than directed
- the smallest effective dose should be used
- do not take longer than 10 days, unless directed by a docter

adults and children 12 years and older | - take 1 tablet every 4 to 6 hours while symptoms persist - if pain or fever does not respond to 1 tablet, 2 tablets may be used - do not exceed 6 tablets in 24 hours, unless directed by a doctor.
Children under 12 years | - ask a doctor

Other information

store between 20-25 0c (68-77 0 F).

- do not use if seal under bottle cap imprinted with” SEALED for YOUR PROTECTION” is broken or missing

PRINCIPAL DISPLAY PANEL

Manufactured for:
Marksans Pharma Inc.
Lake Grove, NY11755, USA

Manufactured by:
Marksans Pharma Ltd.
Verna, Goa-403722, India

Repackaged and Distributed by:
Apotheca, Inc.
Phoenix, AZ 85006

Repackaged and Distributed for:

RejuviLife

Phoenix, AZ 85015

NDC 12634-518-74

IBUPROFEN

MAXIMUM STRENGTH

WITHOUT A PRESCRIPTION

BROWN COATED TABLETS

Pain Reliver

Fever Reducer

RejuviLife®

24 TABLETS 200MG